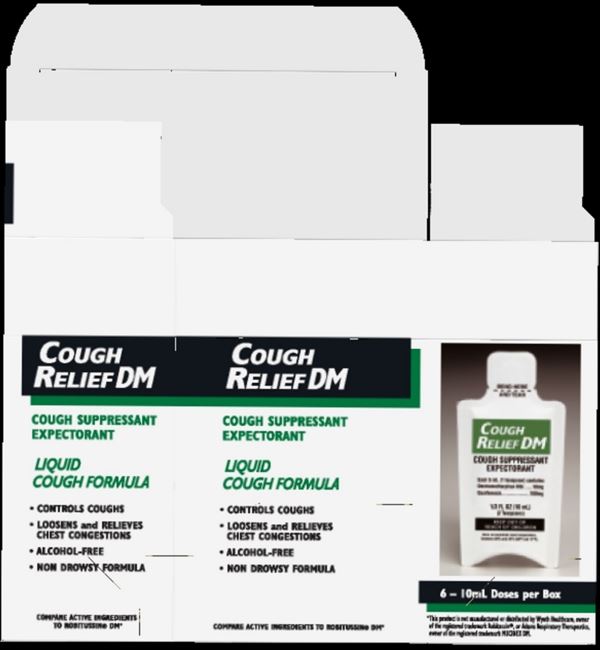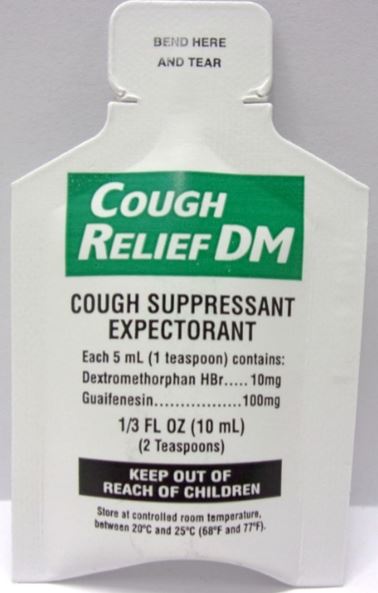 DRUG LABEL: First Aid Direct Cough Relief DM
NDC: 42961-121 | Form: SYRUP
Manufacturer: Cintas Corporation
Category: otc | Type: HUMAN OTC DRUG LABEL
Date: 20220810

ACTIVE INGREDIENTS: GUAIFENESIN 100 mg/5 mL; DEXTROMETHORPHAN HYDROBROMIDE 10 mg/5 mL
INACTIVE INGREDIENTS: CITRIC ACID MONOHYDRATE; FD&C RED NO. 40; GLYCERIN; PROPYLENE GLYCOL; SODIUM CITRATE; SUCRALOSE; PROPYLPARABEN; METHYLPARABEN; WATER

First Aid Direct Cough Relief

Active ingredients (each 5mL/1 teaspoon)

- Dextromethorphan HBr 10mg
- Guaifenesin 100 mg

Purposes

cough suppressant

expectorant

Uses

temporarily:

- relieves coughing due to minor throat and bronchial irritation as may occur with a cold
- helps loosen phlegm (mucus) and thin bronchial secretions to make coughs more productive

Warnings

Do not use

this product for persistent or chronic cough such as occurs with smoking, asthma, emphysema or if cough is accompanied by excessive phlegm (mucus) unless directed by a doctor. Do not use if you are now taking a prescription monoamine oxidase inhibitor (MAOI) (certain drugs for depression, psychiatric or emotional conditions, or Parkinson's disease), or for 2 weeks after stopping the MAOI drug. If you are uncertain whether your prescription drug contains an MAOI, consult a health professional before taking this product.

Stop use and ask doctor if

- cough persists for more than 1 week, tends to recur or is accompanied by fever, rash or persistent headache. A persistent cough may be a sign of a serious condition.

If pregnant or breast-feeding,

ask a health professional before use.

Keep out of reach of children.

In case of overdose, get medical help or contact a Poison Control Center right away.

Directions

do not take more than 6 doses in 24 hours, or as directed by a doctor.

- adults and children 12 years and over, take one premeasured single dose dispenser (2 teaspoons) every 4 hours
- children 6-11 years, measure out and take only 1 teaspoon every 4 hours
- children 2 to 5 years, measure out and take only 1/2 teaspoon every 4 hours
- children under 2 years, consult your doctor

Other information

- do not use if dispenser is torn, cut or opened
- store at room temperature
- avoid excessive heat and humidity

Inactive ingredients

citric acid, FD&C red 40, flavor, glycerin, methyl paraben, propylene glycol, propyl paraben, purified water, sodium citrate, sucralose

Questions?

1-800-327-2704

Package Label Principal Display Panel Single Dose Pack

BEND HERE

AND TEAR

Cough Relief DM

COUGH SUPPRESSANT EXPECTORANT

1/3 FL OZ (10 mL)

(2 Teaspoons)

Package Label Principal Display Panel Box

Cough Relief DM

COUGH SUPPRESSANT

EXPECTORANT

LIQUID COUGH FORMULA

- CONTROLS COUGHS
- LOOSENS and RELIEVES CHEST CONGESTIONS
- ALCOHOL-FREE
- NON DROWSY FORMULA

6-10mL Doses per Box